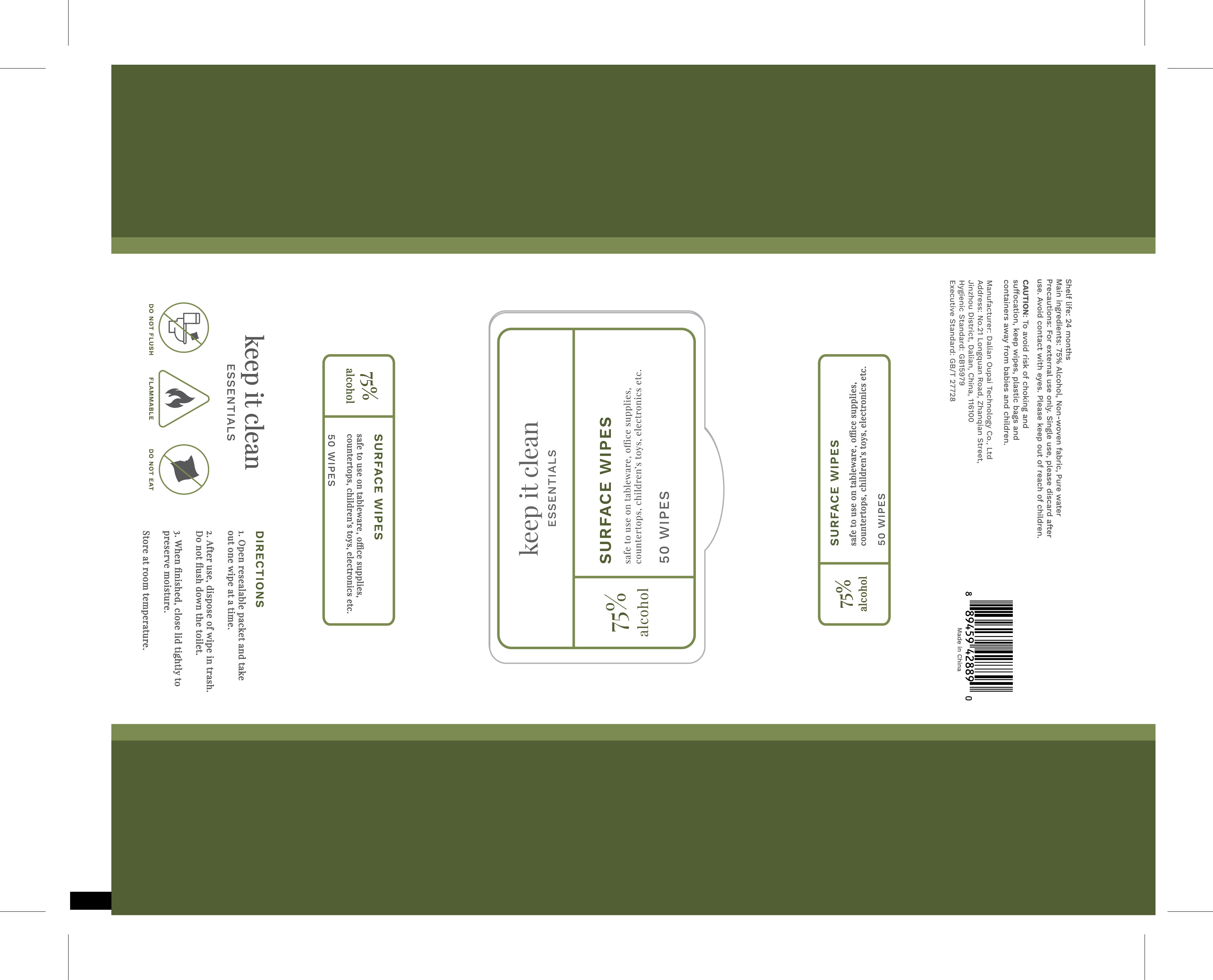 DRUG LABEL: 75% Alcohol Wipes
NDC: 78055-007 | Form: CLOTH
Manufacturer: Dalian Oupai Technology Co.,Ltd
Category: otc | Type: HUMAN OTC DRUG LABEL
Date: 20200707

ACTIVE INGREDIENTS: ALCOHOL 0.75 1/1 1
INACTIVE INGREDIENTS: WATER

75% Alcohol Wet Wipes

Active Ingredient(s)

Alcohol

Purpose

Antiseptic, cleaning

Use

safe to use on tableware,office supplies,countertops,children‘s toys,electronics etc.

Warnings

For external use only.

Do not use

single use,please discard after suse

WHEN USING

Avoid contact with eyes

Stop use and ask a doctor if irritation or rash occurs. These may be signs of a serious condition.

keep out of reach of children

Directions

1.Open resealable packet and take out one wipe at a time.

2.after use,dispose if wipe in trash.donot flush down the tiolet

3.when finised,close lid tightly to preserve moisture

Other information

Store at room temperature

Inactive ingredients

non-woven fabric,pure water